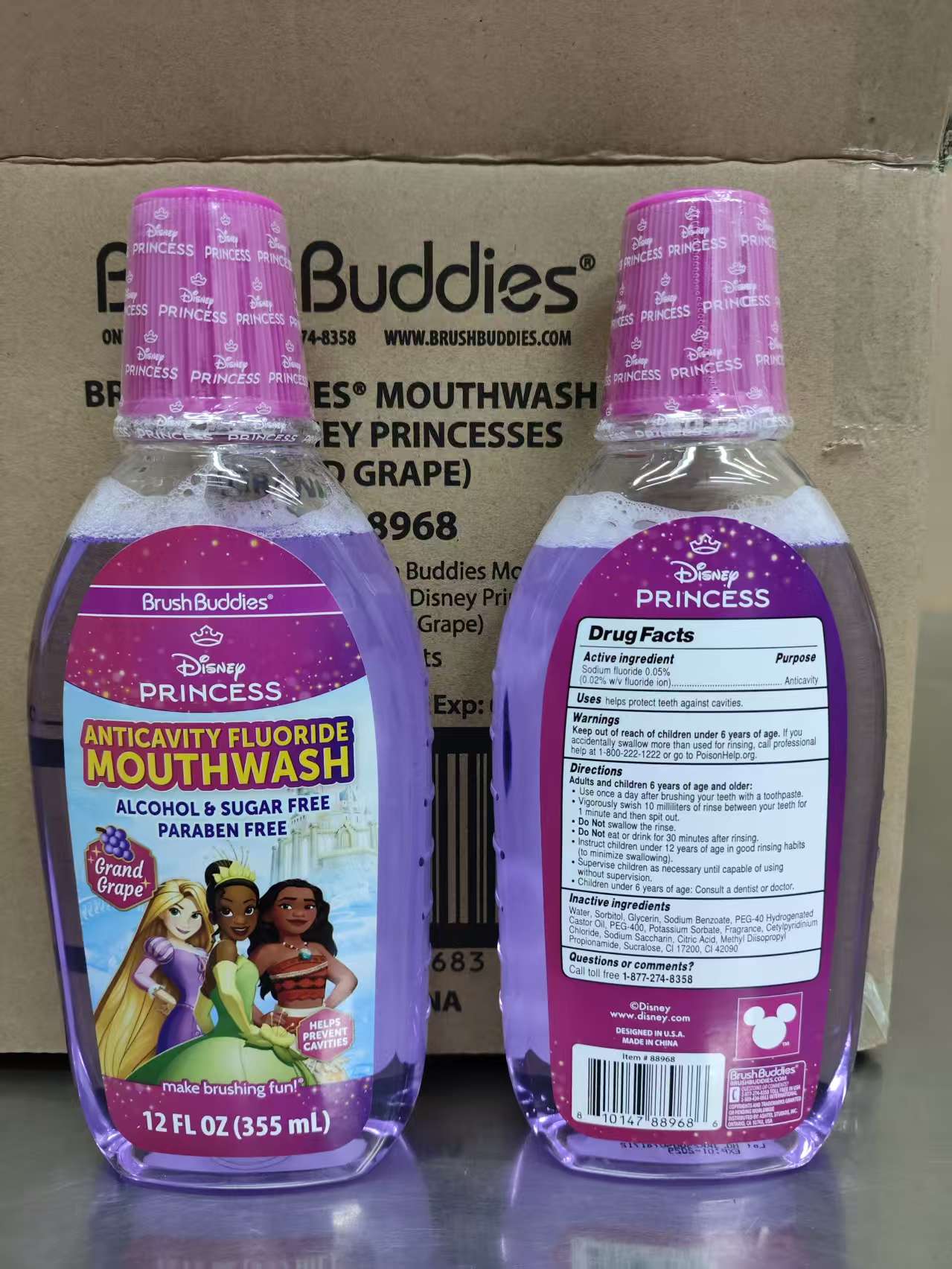 DRUG LABEL: Brush Buddies Mouthwash Disney Princesses Grand Grape
NDC: 73928-133 | Form: LIQUID
Manufacturer: Kingkey MBC Life Technology Group co., LTD.
Category: otc | Type: HUMAN OTC DRUG LABEL
Date: 20260202

ACTIVE INGREDIENTS: SODIUM FLUORIDE 0.05 g/100 mL
INACTIVE INGREDIENTS: SORBITOL; SODIUM BENZOATE; POTASSIUM SORBATE; CETYLPYRIDINIUM CHLORIDE; CITRIC ACID MONOHYDRATE; METHYL SALICYLATE; GLYCERIN; METHYL DIISOPROPYL PROPIONAMIDE; POLYOXYL 40 HYDROGENATED CASTOR OIL; WATER; CI 42090; CI 17200; SACCHARIN SODIUM; FRAGRANCE 13576; PEG-400

73928-133-01 Brush Buddies Mouthwash 12oz - Disney Princesses (Grand Grape)

ACTIVE INGREDIENT

SODIUM FLUORIDE 0.05%

PURPOSE

Anticavity

Keep out of reach of children under 6 years of age

INDICATIONS AND USAGE

Adults and children 6 years of age and older:

Use once a day after brushing your teeth with a toothpaste.

- Vigorously swish 10 milliliters of rinse between your teeth for 1 minute and then split out.
- Do Not swallow the rinse.
- Do Not eat or drink for 30 minutes after rinsing.
- Instruct children under 12 years of age in good rinsing habits(to minimize swallowing).
- Supervise children as necessary until capable of using without supervision.
- Children under 6 years of age: Consult a dentist or doctor.

Keep out of reach of children under 6 years of age, lf you accidentally swallow more than used for rinsing, seek professionalhelp or contact a Poison Control Center immediately. Call professional help at 1-800-222-1222 or go to PoisionHelp.org.

Directions
Adults and children 6 years and older
Use daily after you brush your teeth with toothpaste
Rinse toothpaste from mouth prior to use.
Shake well before each use.Twist and remove cap.
Rinse or gargle for 30 seconds with 15 ml and spit out.
Do Not swallow the rinse.
Do Not eat or drink for 30 minutes after rinsing
Supervise children as necessary.
Children under 6 years of age, consult with a dentist or doctor.

INACTIVE INGREDIENT

Water
SORBITOL
GLYCERIN
SODIUM BENZOATE
PEG-40 HYDROGENATED CASTOR OIL
PEG-400
POTASSIUM SORBATE
Fragrance
CETYLPYRIDINIUM CHLORIDE
SODIUM SACCHARIN
CITRIC ACID
METHYL DIISOPROPYL PROPIONAMIDE
SUCRALOSE
CI 42090
CI 17200